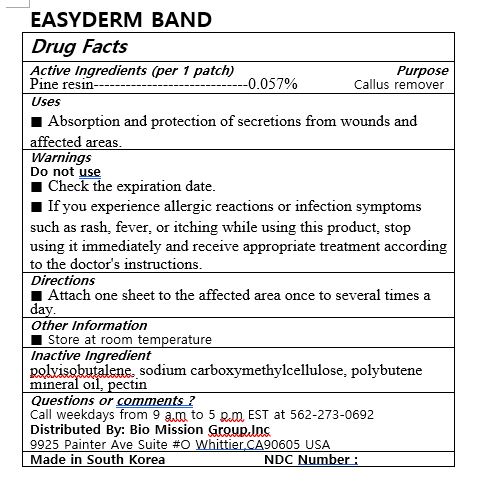 DRUG LABEL: EASYDERM BAND
NDC: 72988-0037 | Form: PATCH
Manufacturer: Lydia Co., Ltd.
Category: otc | Type: HUMAN OTC DRUG LABEL
Date: 20230211

ACTIVE INGREDIENTS: PINUS HALEPENSIS RESIN 0.57 mg/100 mg
INACTIVE INGREDIENTS: PECTIN; CARBOXYMETHYLCELLULOSE

ACTIVE INGREDIENT

pine resin

PURPOSE

Absorption and protection of secretions from wounds and affected areas

Keep out of reach of children

INDICATIONS AND USAGE

Attach one sheet to the affected area once to several times a day.

WARNINGS

■ Check the expiration date.

■ If you experience allergic reactions or infection symptoms such as rash, fever, or itching while using this product, stop using it immediately and receive appropriate treatment according to the doctor's instructions.

INACTIVE INGREDIENT

polyisobutalene, sodium carboxymethylcellulose, polybutene mineral oil, pectin

DOSAGE AND ADMINISTRATION

for external use only